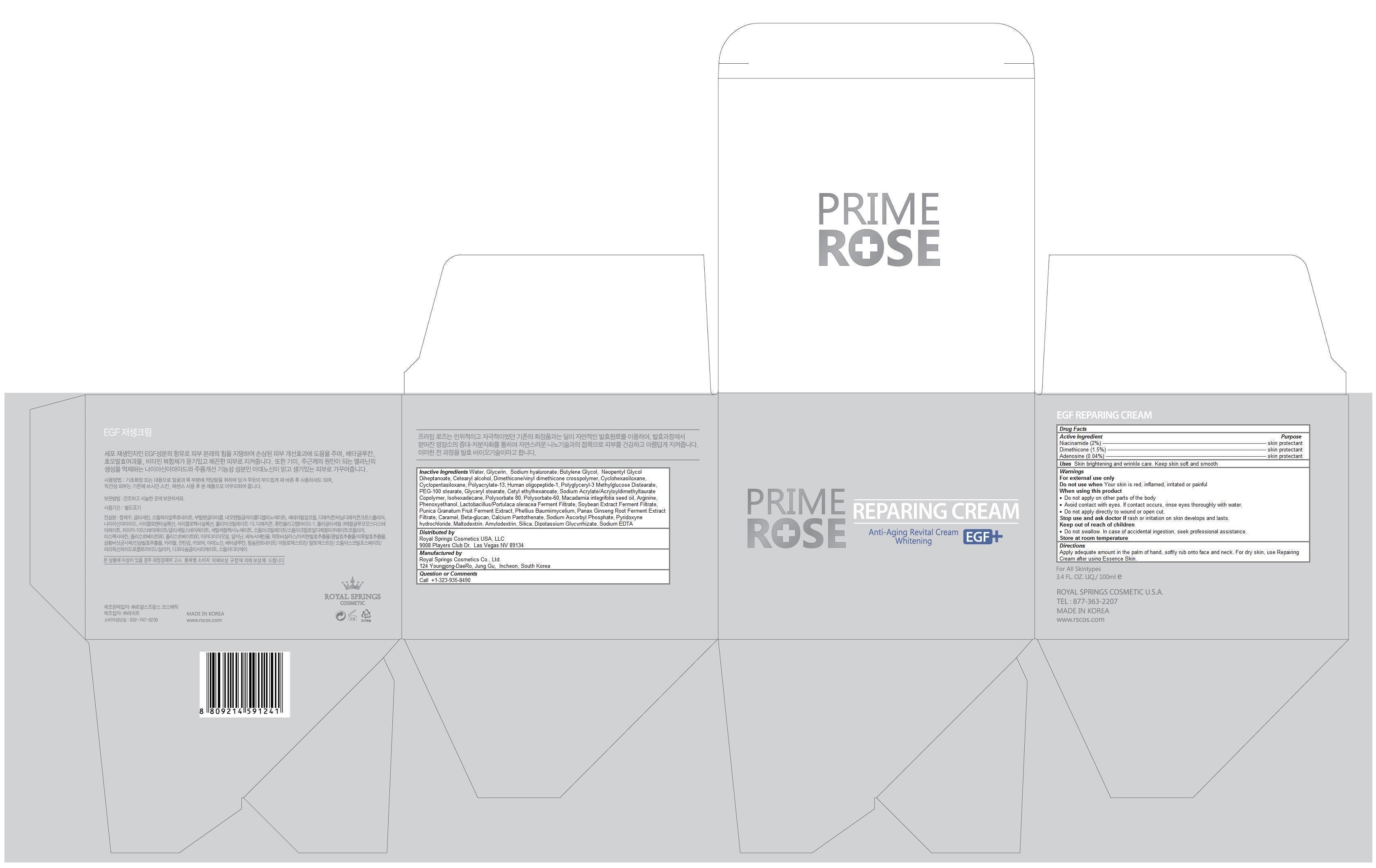 DRUG LABEL: PRIMEROSE EGF
NDC: 69888-102 | Form: CREAM
Manufacturer: Royal Springs Cosmetics USA, LLC
Category: otc | Type: HUMAN OTC DRUG LABEL
Date: 20190115

ACTIVE INGREDIENTS: NIACINAMIDE 0.02 1/100 mL; DIMETHICONE 0.015 1/100 mL; ADENOSINE 0.0004 1/100 mL
INACTIVE INGREDIENTS: WATER; GLYCERIN; HYALURONATE SODIUM; BUTYLENE GLYCOL; NEOPENTYL GLYCOL DIHEPTANOATE; CETOSTEARYL ALCOHOL; DIMETHICONE/VINYL DIMETHICONE CROSSPOLYMER (SOFT PARTICLE); CYCLOMETHICONE 6; CYCLOMETHICONE 5; POLYACRYLAMIDE (10000 MW); PEG-100 STEARATE; GLYCERYL MONOSTEARATE; CETYL ETHYLHEXANOATE; ISOHEXADECANE; POLYSORBATE 80; POLYSORBATE 60; MACADAMIA OIL; ARGININE; PHENOXYETHANOL; ASIAN GINSENG; POMEGRANATE; CARAMEL; CALCIUM PANTOTHENATE; SODIUM ASCORBYL PHOSPHATE; PYRIDOXINE HYDROCHLORIDE; MALTODEXTRIN; AMYLOPECTIN; SILICON DIOXIDE; GLYCYRRHIZINATE DIPOTASSIUM; EDETATE SODIUM

PRIMEROSE EGF REPAIRING CREAM

Active ingredients

Niacinamide (2%)
Dimethicone (1.5%)
Adenosine (0.04%)

Purpose

skin protectant

Keep out of reach of children

- Do not swallow. In case of accidental ingestion, seek professional assistance.

Uses

Skin brightening and wrinkle care. Keep skin soft and smooth.

Warnings

For external use only
Do not use when Your skin is red, inflamed, irritated or painful
When using this product
- Do not apply on other parts of the body
- Avoid contact with eyes. If contact occurs, rinse eyes thoroughly with water.
- Do not apply directly to wound or open cut.
Stop use and ask doctor if rash or irritation on skin develops and lasts.
Store at room temperature

Directions

Apply adequate amount in the palm of hand, softly rub onto face and neck. For dry skin, use Repairing Cream after using Essence Skin.

Inactive ingredients

Water, Glycerin, Sodium hyaluronate, Butylene Glycol, Neopentyl Glycol Diheptanoate, Cetearyl alcohol, Dimethicone/vinyl dimethicone crosspolymer, Cyclohexasiloxane, Cyclopentasiloxane, Polyacrylate-13, Human oligopeptide-1, Polyglyceryl-3 Methylglucose Distearate, PEG-100 stearate, Glyceryl stearate, Cetyl ethylhexanoate, Sodium Acrylate/Acryloyldimethyltaurate Copolymer, Isohexadecane, Polysorbate 80, Polysorbate-60, Macadamia integrifolia seed oil, Arginine, Phenoxyethanol, Lactobacillus/Portulaca oleracea Ferment Filtrate, Soybean Extract Ferment Filtrate, Punica Granatum Fruit Ferment Extract, Phellius Baumiimycelium, Panax Ginseng Root Ferment Extract Filtrate, Caramel, Beta-glucan, Calcium Pantothenate, Sodium Ascorbyl Phosphate, Pyridoxyne hydrochloride, Maltodextrin, Amylodextrin, Silica, Dipotassium Glycyrrhizate, Sodium EDTA